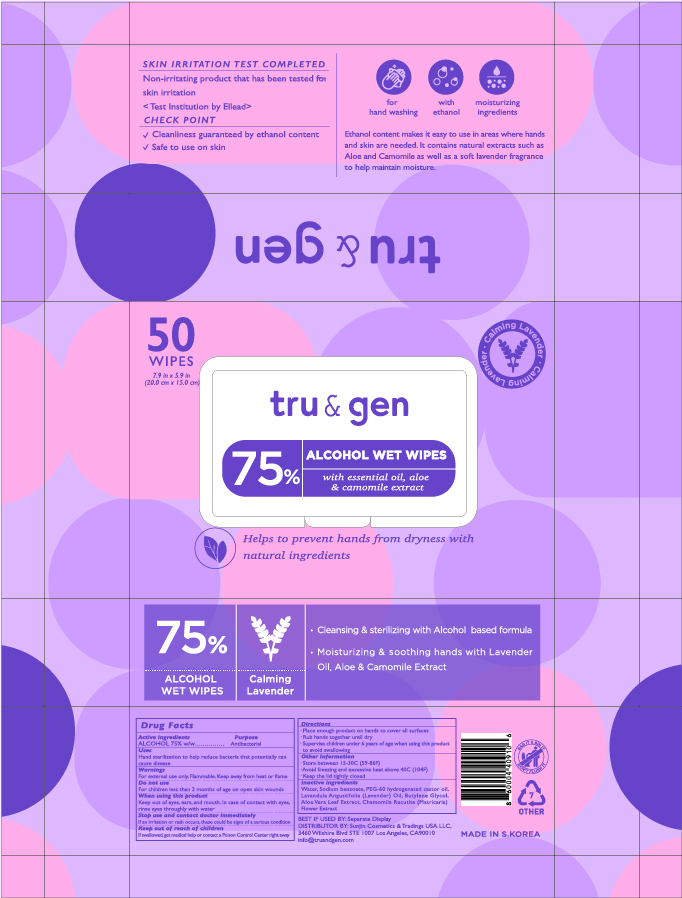 DRUG LABEL: Tru and Gen
NDC: 75773-575 | Form: CLOTH
Manufacturer: Perfumeholic Inc
Category: otc | Type: HUMAN OTC DRUG LABEL
Date: 20200928

ACTIVE INGREDIENTS: ALCOHOL 0.75 1/1 1
INACTIVE INGREDIENTS: BUTYLENE GLYCOL; WATER; ALOE VERA LEAF; CHAMOMILE; PEG-60 HYDROGENATED CASTOR OIL; LAVENDER OIL; SODIUM BENZOATE

Perfumeholic Inc | Tru and Gen | 75773-575-50 | 50 WIPES